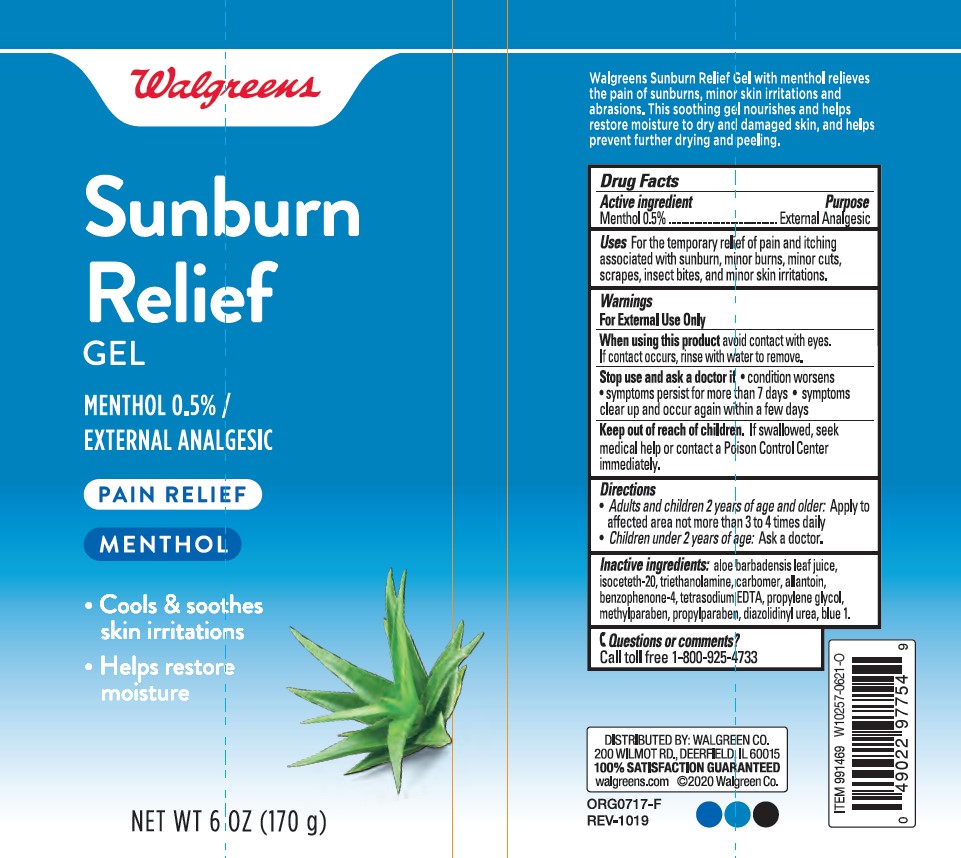 DRUG LABEL: Walgreens Sunburn Relief
NDC: 0363-0966 | Form: GEL
Manufacturer: WALGREEN COMPANY
Category: otc | Type: HUMAN OTC DRUG LABEL
Date: 20241014

ACTIVE INGREDIENTS: MENTHOL 5 mg/1 g
INACTIVE INGREDIENTS: ALOE VERA LEAF; ISOCETETH-20; TROLAMINE; CARBOMER HOMOPOLYMER TYPE C (ALLYL PENTAERYTHRITOL CROSSLINKED); SULISOBENZONE; EDETATE SODIUM; PROPYLENE GLYCOL; METHYLPARABEN; PROPYLPARABEN; DIAZOLIDINYL UREA; FD&C BLUE NO. 1; ALLANTOIN; WATER

Walgreens Sunburn Relief Gel

Active Ingredients

Menthol 0.5%

Purpose

External Analgesic

Uses

For the temporary relief of pain and itching associated with sunburn, minor burns, minor cuts, scrapes, insect bites, and minor skin irritations.

Warnings

For External Use Only

When using this product

avoid contact with eyes. If contact occurs, rinse with water to remove.

Stop use and ask a doctor if

- condition worsens
- symptoms persist for more than 7 days
- symptoms clear up and occur again within a few days

Keep out of reach of children

- If swallowed, seek medical help or contact a Poison Control Center immediately.

Directions

- Adults and children 2 years of age and older: Apply to affected area not more than 3 to 4 times daily
- Children under 2 years of age: Ask a doctor.

Inactive Ingredients:

aloe barbadensis leaf juice, isoceteth-20, triethanolamine, carbomer, allantoin, benzophenone-4, tetrasodium EDTA, propylene glycol, methylparaben, propylparaben, diazolidinyl urea, blue 1, water.